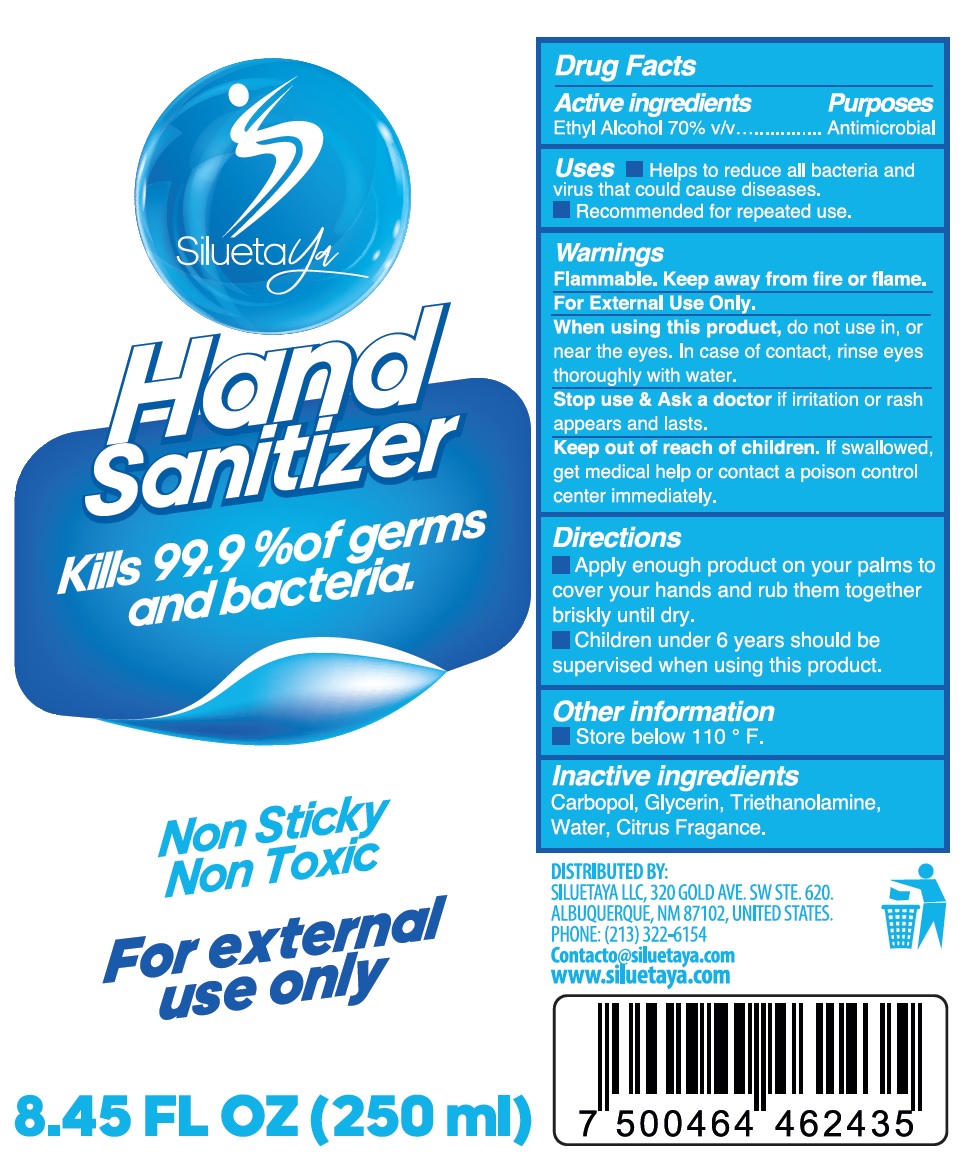 DRUG LABEL: SiluetaYa Hand Sanitizer
NDC: 80916-001 | Form: GEL
Manufacturer: Jp Inter Trade, S.A. de C.V.
Category: otc | Type: HUMAN OTC DRUG LABEL
Date: 20201110

ACTIVE INGREDIENTS: ALCOHOL 0.7 mL/1 mL
INACTIVE INGREDIENTS: CARBOMER HOMOPOLYMER, UNSPECIFIED TYPE; GLYCERIN; TROLAMINE; WATER

SiluetaYa Hand Sanitizer

Active ingredients

Ethyl Alcohol 70% v/v

Purposes

Antimicrobial

Uses

- Helps to reduce all bacteria and virus that could cause diseases.
- Recommended for repeated use.

Warnings

Flammable. Keep away from fire or flame.

For Extract Use Only.

When using this product,

do not use in, or near the eyes. In case of contact, rinse eyes thoroughly with water.

Stop use & Ask a doctor

if irritation or rash appears and lasts.

Keep out of reach of children.

If swallowed, get medical help or contact a poison control center immediately.

Directions

- Apply enough product on your palms to cover your hands and rub them together briskly until dry.
- Children under 6 years should be supervised when using this product.

Other information

- Store below 110 ° F.

Inactive ingredients

Carbopol, Glycerin, Triethanolamine, Water, Citrus Fragrance.